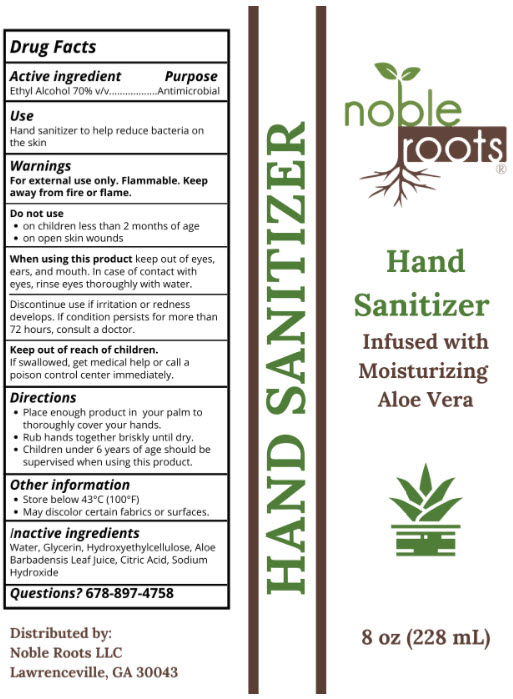 DRUG LABEL: Hand Sanitizer
NDC: 76577-010 | Form: GEL
Manufacturer: Noble Roots, LLC
Category: otc | Type: HUMAN OTC DRUG LABEL
Date: 20200612

ACTIVE INGREDIENTS: Alcohol 70 mL/100 mL
INACTIVE INGREDIENTS: Water; Glycerin; Hydroxyethyl Cellulose, Unspecified; Aloe Vera Leaf; Citric Acid Monohydrate; Sodium Hydroxide

Hand Sanitizer

Drug Facts

Active ingredient

Ethyl Alcohol 70% v/v

Purpose

Antimicrobial

Use

Hand sanitizer to help reduce bacteria on the skin

Warnings

For external use only. Flammable. Keep away from fire or flame.

Do not use

- on children less than 2 months of age
- on open skin wounds

When using this product keep out of eyes, ears, and mouth. In case of contact with eyes, rinse eyes thoroughly with water.

STOP USE

Discontinue use if irritation or redness develops. If condition persists for more than 72 hours, consult a doctor.

Keep out of reach of children.

If swallowed, get medical help or call a poison control center immediately.

Directions

- Place enough product in your palm to thoroughly cover your hands.
- Rub hands together briskly until dry.
- Children under 6 years of age should be supervised when using this product.

Other information

- Store below 43°C (100°F)
- May discolor certain fabrics or surfaces.

Inactive ingredients

Water, Glycerin, Hydroxyethylcellulose, Aloe Barbadensis Leaf Juice, Citric Acid, Sodium Hydroxide

Questions?

678-897-4758

Distributed by:
Noble Roots LLC
Lawrenceville, GA 30043

PRINCIPAL DISPLAY PANEL - 228 mL Bottle Label

noble
roots®

Hand
Sanitizer
Infused with
Moisturizing
Aloe Vera

8 oz (228 mL)